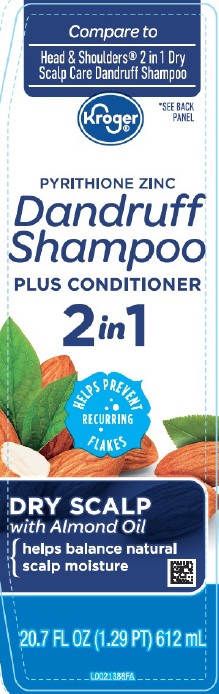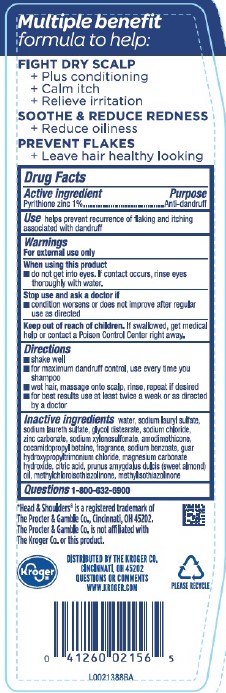 DRUG LABEL: Dry Scalp Care
NDC: 30142-296 | Form: SHAMPOO
Manufacturer: The Kroger Co.
Category: otc | Type: HUMAN OTC DRUG LABEL
Date: 20260227

ACTIVE INGREDIENTS: PYRITHIONE ZINC 10 mg/1 mL
INACTIVE INGREDIENTS: WATER; SODIUM LAURYL SULFATE; SODIUM LAURETH SULFATE; GLYCOL DISTEARATE; SODIUM CHLORIDE; ZINC CARBONATE; SODIUM XYLENESULFONATE; AMODIMETHICONE (800 CST); COCAMIDOPROPYL BETAINE; SODIUM BENZOATE; GUAR HYDROXYPROPYLTRIMONIUM CHLORIDE (1.7 SUBSTITUENTS PER SACCHARIDE); MAGNESIUM CARBONATE HYDROXIDE; CITRIC ACID MONOHYDRATE; ALMOND OIL; METHYLCHLOROISOTHIAZOLINONE; METHYLISOTHIAZOLINONE

Kroger 296.007/296AT-AW
Dry Scalp 2 In 1 Dandruff Shampoo

Claims

Multiple benefit formula to help:

FIGHT DRY SCALP

+ Plus Conditioning

+ Calm itch

+ Relieve irritation

SOOTHE & REDUCE REDNESS

+ Reduce oiliness

PREVENT FLAKES

+ Leave hair healthy looking

Active ingredient

Pyrithione zinc 1%

Purpose

Anti-dandruff

Use

helps prevent recurrence of flaking and itching associated with dandruff

Warnings

For external use only

When using this product

- do not get into eyes. If contact occurs, rinse eyes thoroughly with water.

Stop use and ask a doctor if

- condition worsens or does not improve after regular use as directed

Keep out of reach of children.

if swallowed, get medical help or contact a Poison Control Center right away.

Directions

- shake well
- for maximum dandruff control, use every times you shampoo
- wet hair, massage onto scalp, rinse, repeat if desired
- for best results use at least twice a week or as directed by a doctor

inactive ingredients

water, sodium lauryl sulfate, sodium laureth sulfate, glycol distearate, sodium chloride, zinc carbonate, sodium xylenesulfonate, amodimethicone, cocamidopropyl betaine, fragrance, sodium benzoate, guar hydroxypropyltrimonium chloride, magnesium carbonate hydroxide, citric acid, Prunus amygdalus dulcis (sweet almond) oil, methylchloroisothiazolinone, methylisothiazolinone

Questions

1-800-632-6900

Disclaimer

*Head & Shoulders®is a registered trademark of The Procter & Gamble Co., Cincinnati, OH 45202.

The Procter & Gamble Co. is not affiliated with The Kroger Co. or this product.

Adverse reaction

Kroger

DISTRIBUTED BY THE KROGER CO.,

CINCINNATI, OH 45202

QUESTIONS OR COMMENTS

WWW.KROGER.COM

PLEASE RECYCLE

Principal display panel

Compare to Head & Shoulders®2 in 1 Dry Scalp Care Dandruff Shampoo

Kroger®

*SEE BACK PANEL

PYRITHIONE ZINC

Dandruff Shampoo

PLUS CONDITIONER

2 in 1

HELPS PREVENT REOCCURRING FLAKES

DRY SCALP

with Almond Oil

helps balance natural scalp moisture

20.7 FL OZ (1.29 PT) 612 mL